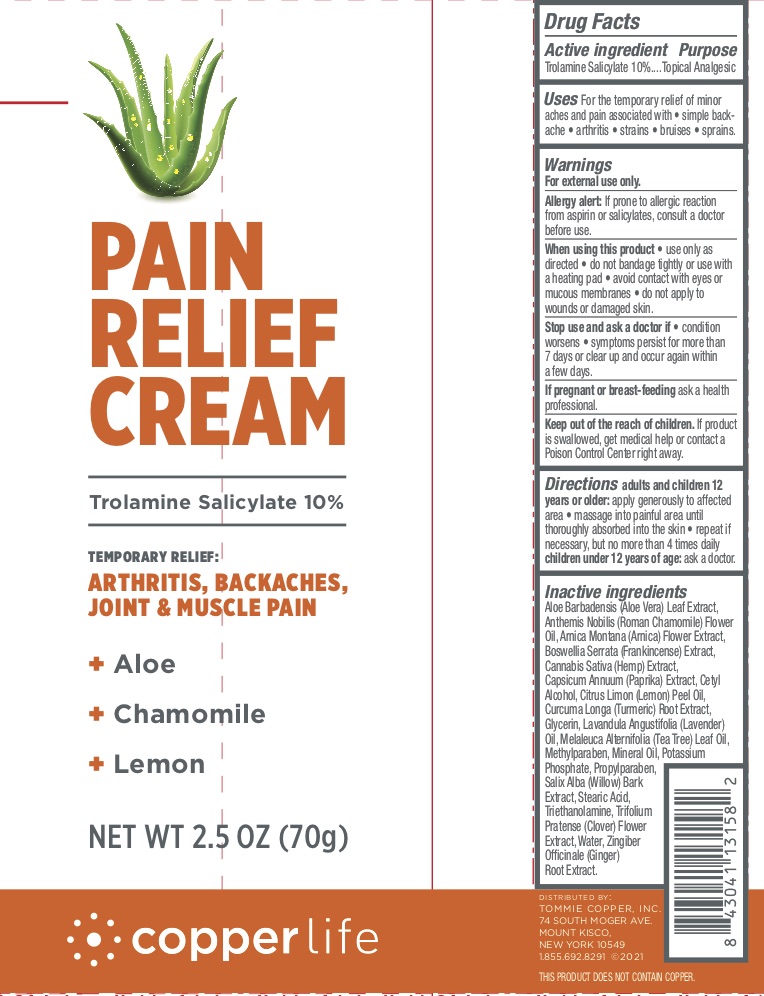 DRUG LABEL: Copperlife Pain Relief
NDC: 72562-123 | Form: CREAM
Manufacturer: Tommie Copper, Inc.
Category: otc | Type: HUMAN OTC DRUG LABEL
Date: 20241215

ACTIVE INGREDIENTS: TROLAMINE SALICYLATE 10 g/100 g
INACTIVE INGREDIENTS: TROLAMINE; MINERAL OIL; METHYLPARABEN; TRIFOLIUM PRATENSE FLOWER; GINGER; SALIX ALBA BARK; PROPYLPARABEN; CHAMAEMELUM NOBILE FLOWER OIL; WATER; POTASSIUM PHOSPHATE, MONOBASIC; STEARIC ACID; GLYCERIN; ALOE VERA LEAF; ISOPROPYL ALCOHOL; INDIAN FRANKINCENSE; CANNABIS SATIVA SEED; CETYL ALCOHOL; ARNICA MONTANA FLOWER; PAPRIKA; LEMON OIL; TURMERIC; TEA TREE OIL; LAVENDER OIL

TC Pain Relief Cream (Copperlife)

ACTIVE INGREDIENT

Trolamine Salicylate 10%

PURPOSE

Topical Analgesic

INDICATIONS AND USAGE

For the temporary relief of minor aches and pain associated with simple backaches, arthritis, strains, bruises, and sprains.

WARNINGS

For external use only. Allergy Alert: If prone to allergic reaction from aspirin or salicylates, consult a doctor before use. . When using this product use only as directed, do not bandage tightly or use with a heating pad, avoid Stop use and ask a doctor if condition worsens, if symptoms persist for more than 7 days or clear up and occur again within a few days.

PREGNANCY OR BREAST FEEDING

If pregnant or breast-feeding ask a health professional.

KEEP OUT OF REACH OF CHILDREN

If swallowed, get medical help or contact a Poison Control Center right away.

DOSAGE AND ADMINISTRATION

Adults and children 12 years of age and older: apply generously to the affected area, massage into painful area until thoroughly absorbed into the skin, repeat if necessary but not more than 4 times daily. Children under 12 years of age: ask a doctor.

INACTIVE INGREDIENT

Aloe Barbadensis (Aloe Vera) Leaf Extract, Anthemis Nobilis (Roman Chamomile) Flower Oil, Arnica Montana (Arnica) Flower Extract, Boswellia Serrata (Frankincense) Extract, Cannabis Sativa (Hemp) Extract, Capsicum Annuum (Paprika) Extract, Cetyl Alcohol, Citrus Limon (Lemon) Peel Oil, Curcuma Longa (Tumeric) Root Extract, Glycerin, Lavandula Angustifolia (Lavender) Oil, Melaleuca Alternifolia (Tea Tree) Leaf Oil, Methylparaben, Mineral Oil, Potassium Phosphate, Propylparaben, Salix Alba (Willow) Bark Extract, Stearic Acid, Triethanolamine, Trifolium Pratense (Clover) Flower Extract, Water, Zingiber Officinale (Ginger) Root Extract.